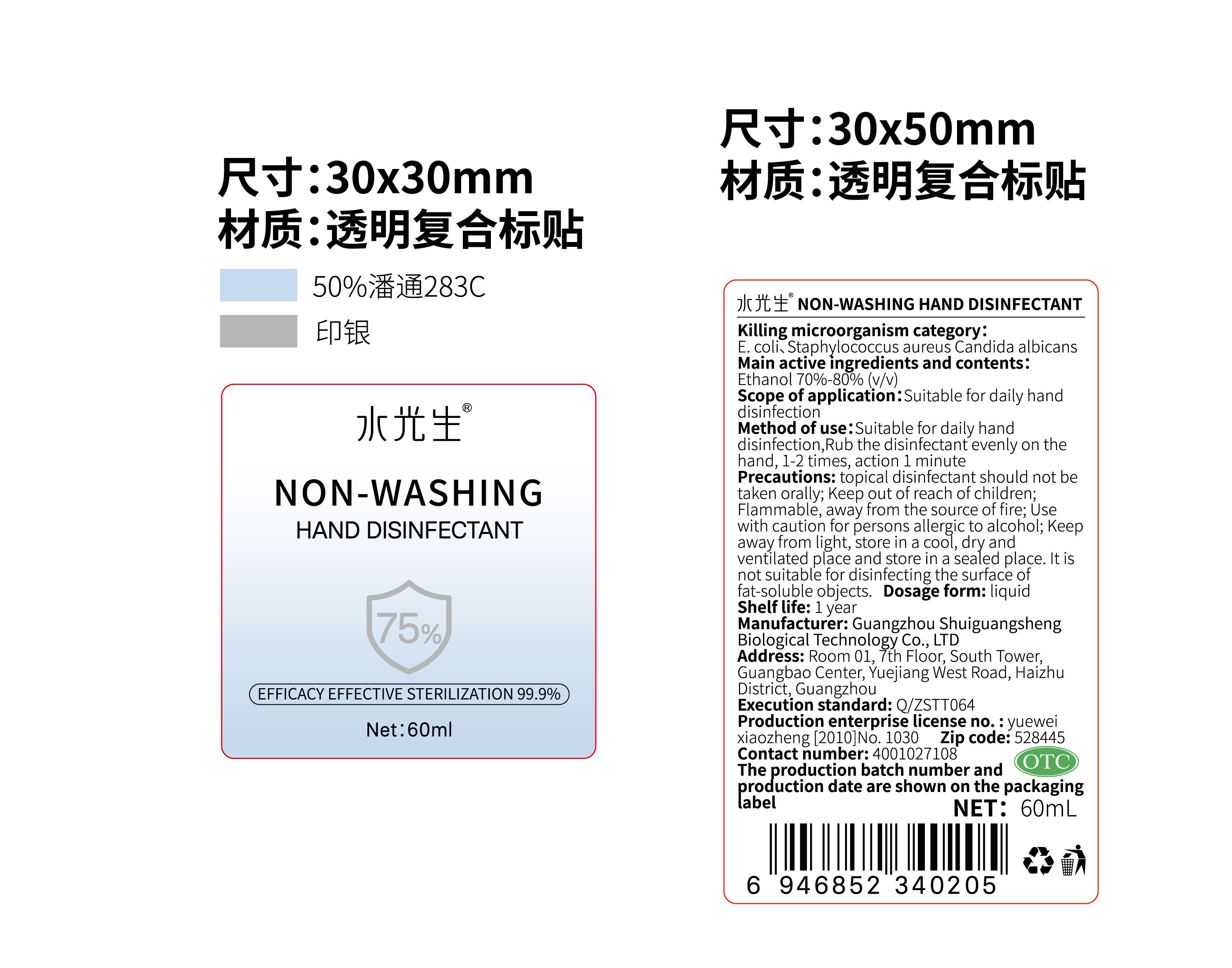 DRUG LABEL: NON-WASHING HAND DISINFECTANT
NDC: 55412-001 | Form: LIQUID
Manufacturer: Guangzhou Shuiguangsheng Biological Technology Co., Ltd.
Category: otc | Type: HUMAN OTC DRUG LABEL
Date: 20200511

ACTIVE INGREDIENTS: ALCOHOL 39.6 mL/60 mL
INACTIVE INGREDIENTS: WATER; TROLAMINE; GLYCERIN; CARBOMER INTERPOLYMER TYPE A (55000 CPS)

DOSAGE AND ADMINISTRATION

Keep away, from light, store in a cool, dry and ventilated place and store in a sealed place.

INACTIVE INGREDIENT

water

glycerin

Acrylic (ester) / C10-30 alkanol acrylate cross-linked polymer

Triethanolamine

INDICATIONS AND USAGE

Suitable for daily hand disinfection,Rub the disinfectant evenly on the hand, 1-2 times, action 1 minute

ACTIVE INGREDIENT

Ethanol

keep out of reach of children

PURPOSE

Disinfection
Sterilization

WARNINGS

topical disinfectant should not be taken orally; Keep out of reach of children;Flammable, away from the source of fire; Use
with caution for persons allergic to alcohol; Keep away, from light, store in a cool, dry and ventilated place and store in a sealed place. It is not suitable for disinfecting the surface of fat-soluble objects.